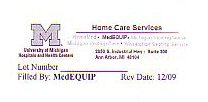 DRUG LABEL: OXYGEN
NDC: 62340-001 | Form: GAS
Manufacturer: University of Michigan Health System dba MedEquip
Category: prescription | Type: HUMAN PRESCRIPTION DRUG LABEL
Date: 20100101

ACTIVE INGREDIENTS: OXYGEN 99 L/100 L

LIQUID CONTAINER LABEL

M

UNIVERSITY OF MICHIGAN HOSPITALS AND HEALTH SYSTEM

HOME CARE SERVICES

HOMEMED MEDEQUIP MICHIGAN VISITING NURSES MICHIGAN VISITING CARE WHEELCHAIR SEATING SERVICE

2850 S. INDUSTRIAL HWY SUITE 300 ANN ARBOR MI 48104

WARNINGS

FILLED BY MEDEQUIP REV DATE 12/09

LOT NUMBER_____________________________